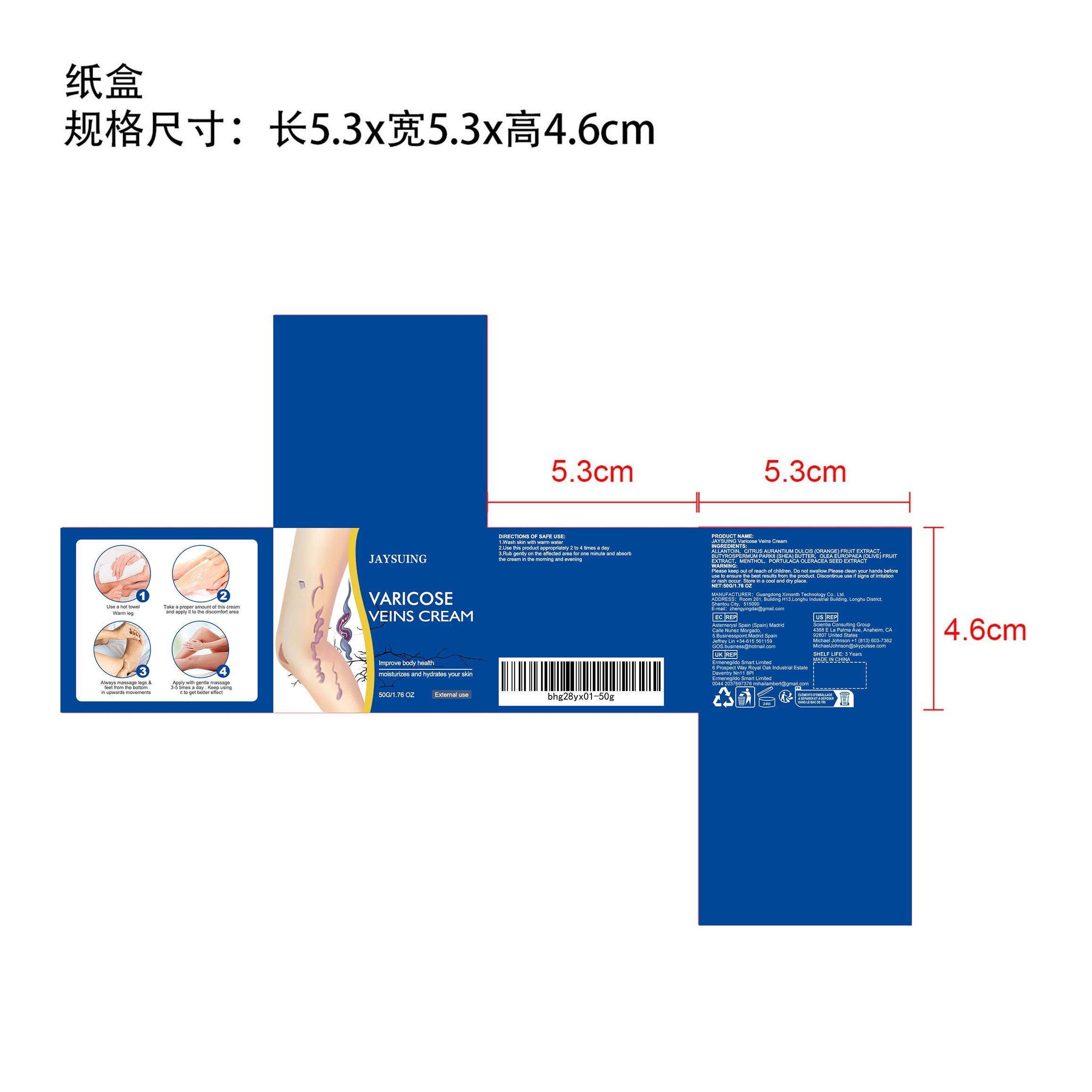 DRUG LABEL: Varicose Veins Cream
NDC: 84660-008 | Form: CREAM
Manufacturer: Guangdong Ximonth Technology Co., Ltd.
Category: otc | Type: HUMAN OTC DRUG LABEL
Date: 20240905

ACTIVE INGREDIENTS: PORTULACA OLERACEA SEED 10.5 g/50 g; BLACK OLIVE 7.5 g/50 g; MENTHOL, UNSPECIFIED FORM 7.5 g/50 g; ORANGE 7.5 g/50 g; SHEA BUTTER 4.5 g/50 g
INACTIVE INGREDIENTS: ALLANTOIN 12.5 g/50 g

Active Ingredient(s)

CITRUS AURANTIUM DULCIS (ORANGE) FRUIT EXTRACT, BUTYROSPERMUM PARKII (SHEA) BUTTER, OLEA EUROPAEA (OLIVE) FRUITIEXTRACT, MENTHOL, PORTULACA OLERACEA SEED EXTRACT

Purpose

Improve the phenomenon of varicose veins

Use

1.Wash skin with warm water.2.Use this product approprlately 2 to 4 times a day.3.Rub gently on the affected area for one minute and absorbdthe cream in the morning and evening.

Warnings

Please keep out of reach of children.Do not swallow.Please clean your hands before use to ensure the best results from the product.Discontinue use if signs of irritation or rash occur.Store in a cool and dry place.

Do not use

Discontinue use if signs of irritation or rash occur.

STOP USE

Discontinue use if signs of irritation or rash occur.

KEEP OUT OF REACH OF CHILDREN

Please keep out of reach of children. Do not swallow.

STORAGE AND HANDLING

Avoid freezing and excessive heat above 40C (104F) ）

Store in a cool and dry place.

INACTIVE INGREDIENT

ALLANTOIN